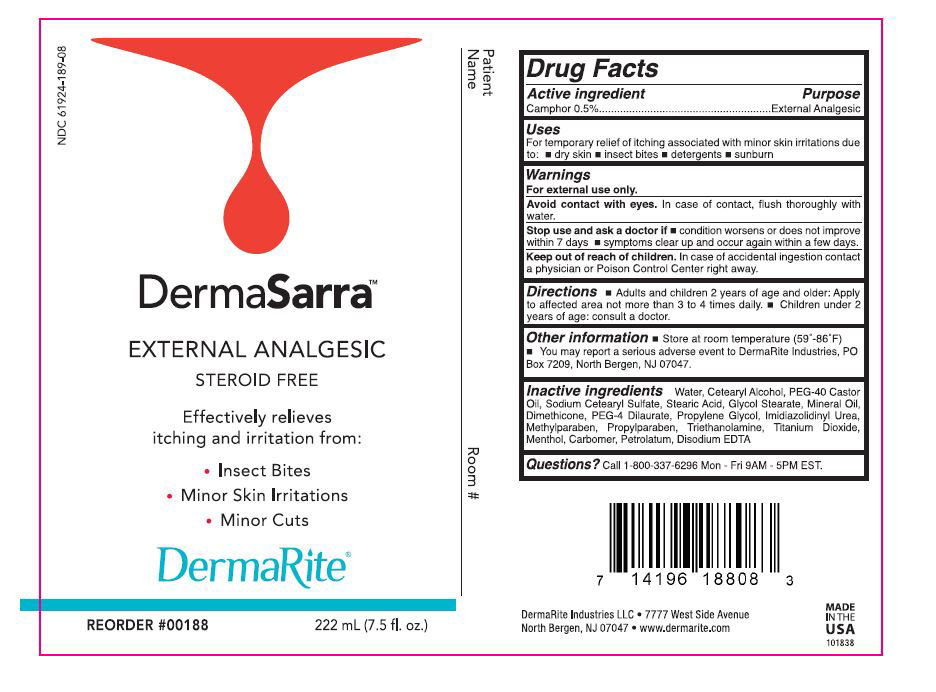 DRUG LABEL: DERMASARRA
NDC: 61924-189 | Form: LOTION
Manufacturer: DERMARITE INDUSTRIES, LLC
Category: otc | Type: HUMAN OTC DRUG LABEL
Date: 20241205

ACTIVE INGREDIENTS: CAMPHOR (NATURAL) 0.005 g/1 mL
INACTIVE INGREDIENTS: CARBOMER HOMOPOLYMER TYPE C; CETOSTEARYL ALCOHOL; IMIDUREA; DIMETHICONE; EDETATE DISODIUM; GLYCOL STEARATE; PEG-40 CASTOR OIL; PEG-4 DILAURATE; PROPYLENE GLYCOL; METHYLPARABEN; MINERAL OIL; PETROLATUM; PROPYLPARABEN; SODIUM CETOSTEARYL SULFATE; STEARIC ACID; TITANIUM DIOXIDE; TROLAMINE; WATER; MENTHOL

DRUG LISTING: DERMASARRA

Active Ingredient

Camphor 0.5%

Purpose

External Analgesic

Uses:

Temporary relief of itching associiated with minor skin irritations due to:

- dry skin
- insect bites
- detergent
- sunburn

Warnings:

- For external use only.
- Avoid contact with eyes. In case of contact, flush thoroughly with water.
- Stop use and ask a doctor if, condition worsens, symptoms last for more than 7 days, symptoms clear up and occur again within a few days
- Do not use on deep puncture wounds, animal bites, or serious burns.

Warnings

- Keep out of reach of children. In case of accidental ingestion contact a physician or Poison Control Center right away

Directions:

Adults and children 2 years of age and older: Apply to affected area not more than 3 to 4 times dialy,

Children under 2 years of age: Consult a doctor

Other Infomation:

Store at room temperature (59°-86°F)

You may report a serious adverse event to DermaRite Industries, PO Box 7209, North Bergen, NJ 07047

Inactive Ingredients:

water, Cetearyl Alcohol, PEG-40 Castor Oil, Sodium Cetearyl Sulfate, Stearic Acid, Glycol Stearate, Mineral Oil, Dimethicone, PEG-4 Dilaurate, Propylene Glycol, Imidazolidinyl Urea, Methylparaben, Propylparaben, Triethanolamine, Titanium Dioxide, menthol, Carbomer, Petrolatum, Disodium EDTA

Questions?

Call 1-800-337-6296 Mon-Fri 9AM-5PM EST.